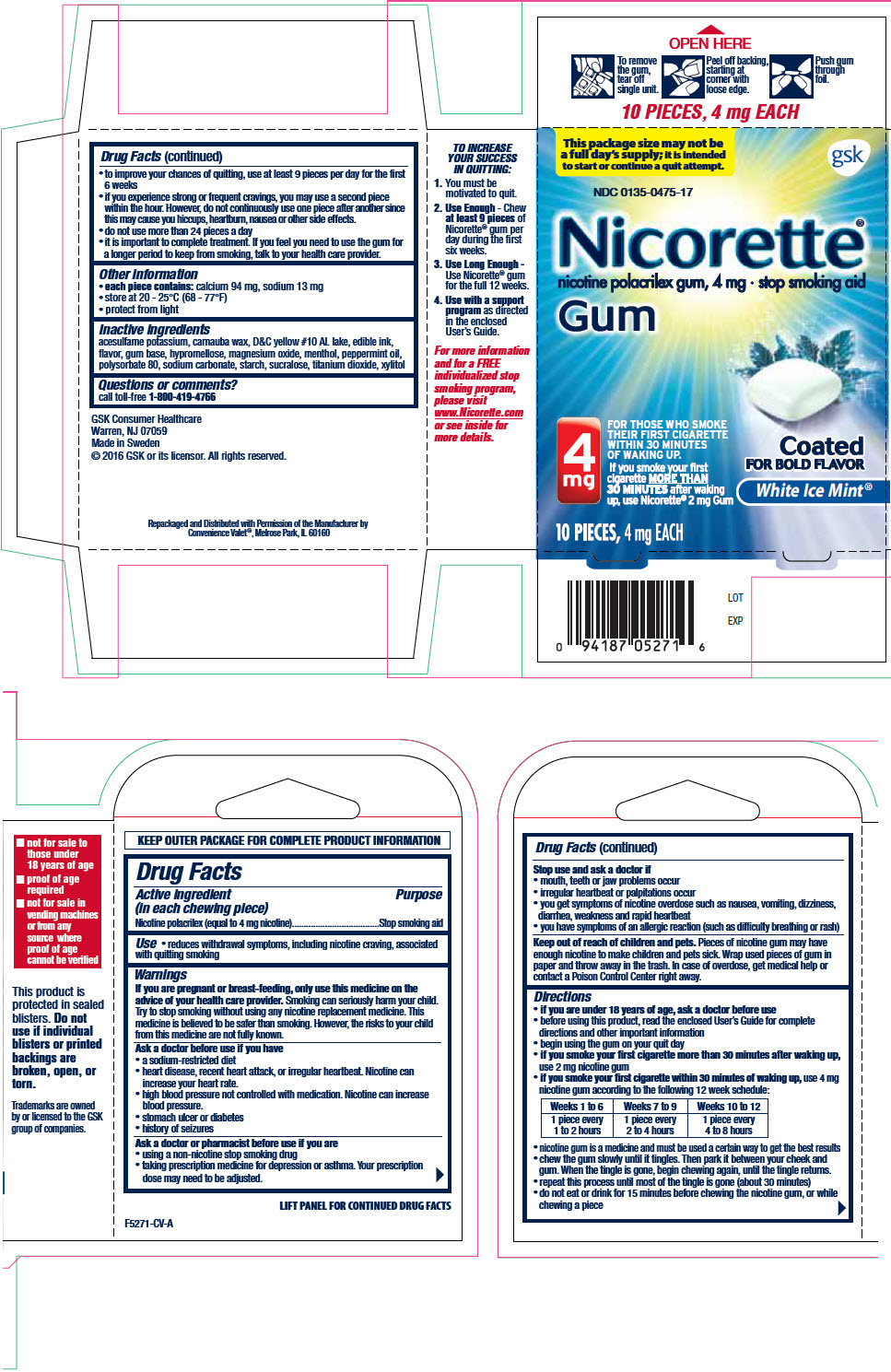 DRUG LABEL: Nicorette White Mint nicotine polacrilex
NDC: 29485-5271 | Form: GUM, CHEWING
Manufacturer: Lil' Drug Store Products, Inc.
Category: otc | Type: HUMAN OTC DRUG LABEL
Date: 20241230

ACTIVE INGREDIENTS: NICOTINE 4 mg/1 1
INACTIVE INGREDIENTS: POLACRILIN; ACESULFAME POTASSIUM; CARNAUBA WAX; HYPROMELLOSE, UNSPECIFIED; MAGNESIUM OXIDE; MENTHOL, UNSPECIFIED FORM; PEPPERMINT OIL; POLYSORBATE 80; SODIUM BICARBONATE; SODIUM CARBONATE; SUCRALOSE; TITANIUM DIOXIDE; XYLITOL

Nicorette® White Mint nicotine polacrilex gum, chewing

Drug Facts

Active ingredient (in each chewing piece)

Nicotine polacrilex (equal to 4 mg nicotine)

Purpose

Stop smoking aid

Use

- reduces withdrawal symptoms, including nicotine craving, associated with quitting smoking

Warnings

PREGNANCY OR BREAST FEEDING

If you are pregnant or breast-feeding, only use this medicine on the advice of your health care provider. Smoking can seriously harm your child. Try to stop smoking without using any nicotine replacement medicine. This medicine is believed to be safer than smoking. However, the risks to your child from this medicine are not fully known.

Ask a doctor before use if you have

- a sodium-restricted diet
- heart disease, recent heart attack, or irregular heartbeat. Nicotine can increase your heart rate.
- high blood pressure not controlled with medication. Nicotine can increase blood pressure.
- stomach ulcer or diabetes
- history of seizures

Ask a doctor or pharmacist before use if you are

- using a non-nicotine stop smoking drug
- taking prescription medicine for depression or asthma. Your prescription dose may need to be adjusted.

Stop use and ask a doctor if

- mouth, teeth or jaw problems occur
- irregular heartbeat or palpitations occur
- you get symptoms of nicotine overdose such as nausea, vomiting, dizziness, diarrhea, weakness and rapid heartbeat
- you have symptoms of an allergic reaction (such as difficulty breathing or rash)

Keep out of reach of children and pets. Pieces of nicotine gum may have enough nicotine to make children and pets sick. Wrap used pieces of gum in paper and throw away in the trash. In case of overdose, get medical help or contact a Poison Control Center right away.

Directions

- if you are under 18 years of age, ask a doctor before use
- before using this product, read the enclosed User's Guide for complete directions and other important information
- begin using the gum on your quit day
- if you smoke your first cigarette more than 30 minutes after waking up, use 2 mg nicotine gum
- if you smoke your first cigarette within 30 minutes of waking up, use 4 mg nicotine gum according to the following 12 week schedule:

Weeks 1 to 6 | Weeks 7 to 9 | Weeks 10 to 12
1 piece every 1 to 2 hours | 1 piece every 2 to 4 hours | 1 piece every 4 to 8 hours

- nicotine gum is a medicine and must be used a certain way to get the best results
- chew the gum slowly until it tingles. Then park it between your cheek and gum. When the tingle is gone, begin chewing again, until the tingle returns.
- repeat this process until most of the tingle is gone (about 30 minutes)
- do not eat or drink for 15 minutes before chewing the nicotine gum, or while chewing a piece
- to improve your chances of quitting, use at least 9 pieces per day for the first 6 weeks
- if you experience strong or frequent cravings, you may use a second piece within the hour. However, do not continuously use one piece after another since this may cause you hiccups, heartburn, nausea or other side effects.
- do not use more than 24 pieces a day
- it is important to complete treatment. If you feel you need to use the gum for a longer period to keep from smoking, talk to your health care provider.

Other information

- each piece contains: calcium 94 mg, sodium 13 mg
- store at 20 - 25°C (68 - 77°F)
- protect from light

Inactive ingredients

acesulfame potassium, carnauba wax, D&C yellow #10 Al. lake, edible ink, flavor, gum base, hypromellose, magnesium oxide, menthol, peppermint oil, polysorbate 80, sodium carbonate, starch, sucralose, titanium dioxide, xylitol

Questions or comments?

call toll-free 1-800-419-4766

Repackaged and Distributed with Permission of the Manufacturer by
Convenience Valet®, Melrose Park, IL 60160

PRINCIPAL DISPLAY PANEL - 10 Piece Blister Pack Carton

This package size may not be
a full day's supply; it is intended
to start or continue a quit attempt.

NDC 0135-0475-17

gsk

Nicorette®
nicotine polacrilex gum, 4 mg • stop smoking aid
Gum

4
mg

FOR THOSE WHO SMOKE
THEIR FIRST CIGARETTE
WITHIN 30 MINUTES
OF WAKING UP.

If you smoke your first
cigarette MORE THAN
30 MINUTES after waking
up, use Nicorette® 2 mg Gum

Coated
FOR BOLD FLAVOR

White Ice Mint®

10 PIECES, 4 mg EACH